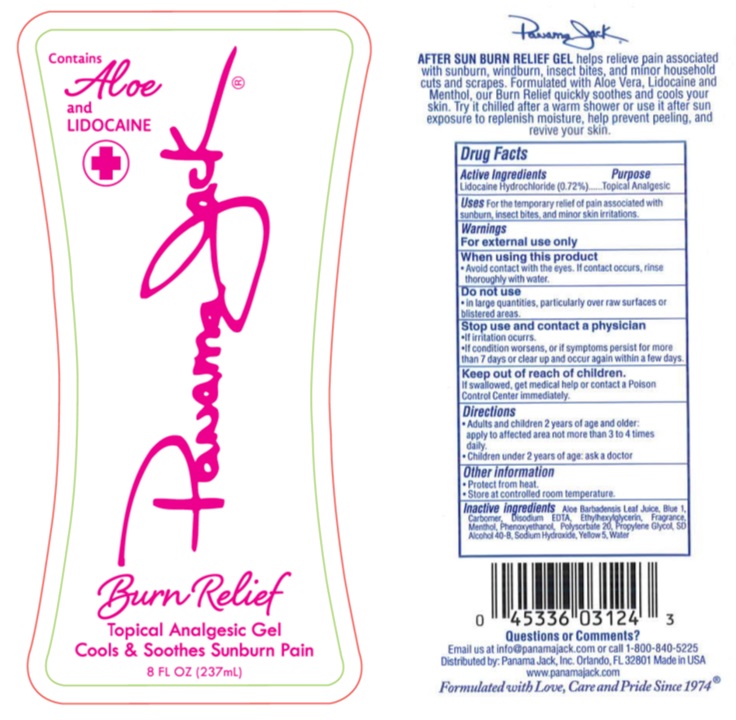 DRUG LABEL: Panama Jack
NDC: 58443-0261 | Form: GEL
Manufacturer: Prime Enterprises Inc.
Category: otc | Type: HUMAN OTC DRUG LABEL
Date: 20200117

ACTIVE INGREDIENTS: LIDOCAINE HYDROCHLORIDE 7.128 mg/1 mL
INACTIVE INGREDIENTS: ALOE VERA LEAF; CARBOXYPOLYMETHYLENE; EDETATE DISODIUM; MENTHOL; PHENOXYETHANOL; ETHYLHEXYLGLYCERIN; POLYSORBATE 20; ALCOHOL; SODIUM HYDROXIDE; FD&C YELLOW NO. 5; WATER; FD&C BLUE NO. 1; PROPYLENE GLYCOL

Panama Jack Burn Relief Gel with Aloe Vera and Lidocaine

Active Ingredients

Lidocaine Hydrochloride (0.72%)

Purpose

Topical Analgesic

Uses

For the temporary relief of pain associated with sunburn, insect bites and minor skin irritations.

Warnings

For external use only

Do not use on damaged or broken skin

When using this product keep out of eyes. Rinse with water to remove

Stop use and ask a doctor if rash occurs

Keep out of reach of children. If product is swallowed, get medical help or contact a Poison Control Center right away.

When using this product

- Avoid contact with the eyes. If contact occurs, rinse thoroughly with water.

Do not use

- in large quantities, particularly over raw surfaces or blistered areas.

Stop use and contact a physician

- If irritation occures.
- If condition worsens, or if symptoms persist for more than 7 days or clear up and occur again within a few days.

Keep out of reach of children.

If swallowed, get medical help or contact a Poison Control Center immediately.

Directions

- Adults and children 2 years of age and older: apply to affected area not more than 3 to 4 times daily.
- Children under 2 years of age: ask a doctor

Other Information

- Protect from heat.
- Store at controlled room temperature.

Inactive Ingredients

Aloe Barbadensis Leaf Juice, Blue 1, Carbomer, Disodium EDTA, Ethylhexylglycerin, Fragrance, Menthol, Phenoxyethanol, Polysorbate 20, Propylene Glycol, SD Alcohol 40-B, Sodium Hydroxide, Yellow 5, Water